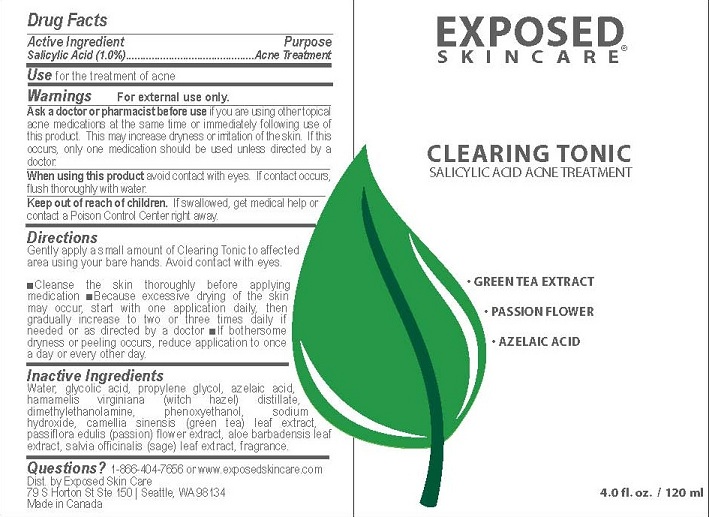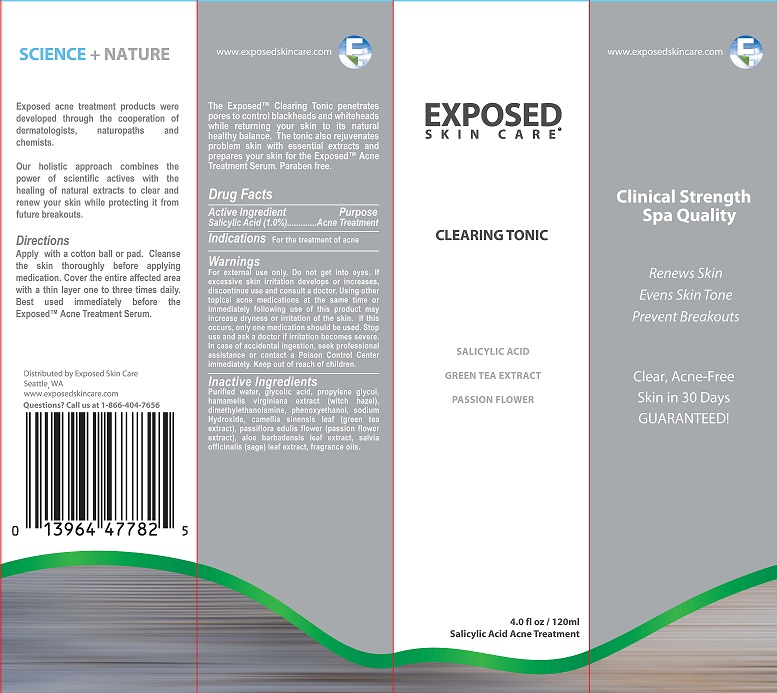 DRUG LABEL: CLEARING TONIC
NDC: 55878-104 | Form: LIQUID
Manufacturer: Halogent, LLC (DBA Exposed Skin Care) 
Category: otc | Type: HUMAN OTC DRUG LABEL
Date: 20130313

ACTIVE INGREDIENTS: SALICYLIC ACID 1 g/100 mL
INACTIVE INGREDIENTS: WATER; GLYCOLIC ACID; PROPYLENE GLYCOL; AZELAIC ACID; HAMAMELIS VIRGINIANA ROOT BARK/STEM BARK; DEANOL; PHENOXYETHANOL; SODIUM HYDROXIDE; CAMELLIA SINENSIS WHOLE; HYDROGENATED POLYDECENE (550 MW); TRIDECETH-6; FILIPENDULA ULMARIA FLOWER; LICORICE; OCIMUM BASILICUM FLOWERING TOP; CAMELLIA SINENSIS WHOLE; PASSIFLORA EDULIS FLOWER; ALOE VERA LEAF; SALVIA OFFICINALIS FLOWERING TOP

PURPOSE

ACNE TREATMENT

ACTIVE INGREDIENT

SALICYLIC ACID (1%)

WARNINGS FOR EXTERNAL USE ONLY

USE

FOR THE TREATMENT OF ACNE

Ask a doctor or pharmacist before use if you are using other topical acne medications at the same time or immediately following use of this product. This may increase dryness or irritation of the skin. If this occurs, only one medication should be used unless directed by a doctor.

Keep out of reach of children. If swallowed, get medical help or contact a Poison Control Center right away.

When using this product avoid contact with eyes. If contact occurs, flush thoroughly with water.

Directions

Gently apply a small amount of Clearing Tonic to affected area using your bare hands. Avoid contact with eyes.

- Cleanse the skin thoroughly before applying medication
- Because excessive drying of the skin may occur, start with one application daily, then gradually increase to two or three times daily if needed or as directed by a doctor
- If bothersome dryness or peeling occurs, reduce application to once a day or every other day.

Inactive Ingredients

Water, glycolic acid, propylene glycol, azelaic acid, hamamelis virginiana (witch hazel) distillate, dimethylethanolamine, phenoxyethanol, sodium hydroxide, camellia sinensis (green tea) leaf extract, passiflora edulis (passion) flower extract, aloe barbadensis leaf extract, salvia officinalis (sage) leaf extract, fragrance.

QUESTIONS

Questions? 1-866-404-7656 or www.exposedskincare.com